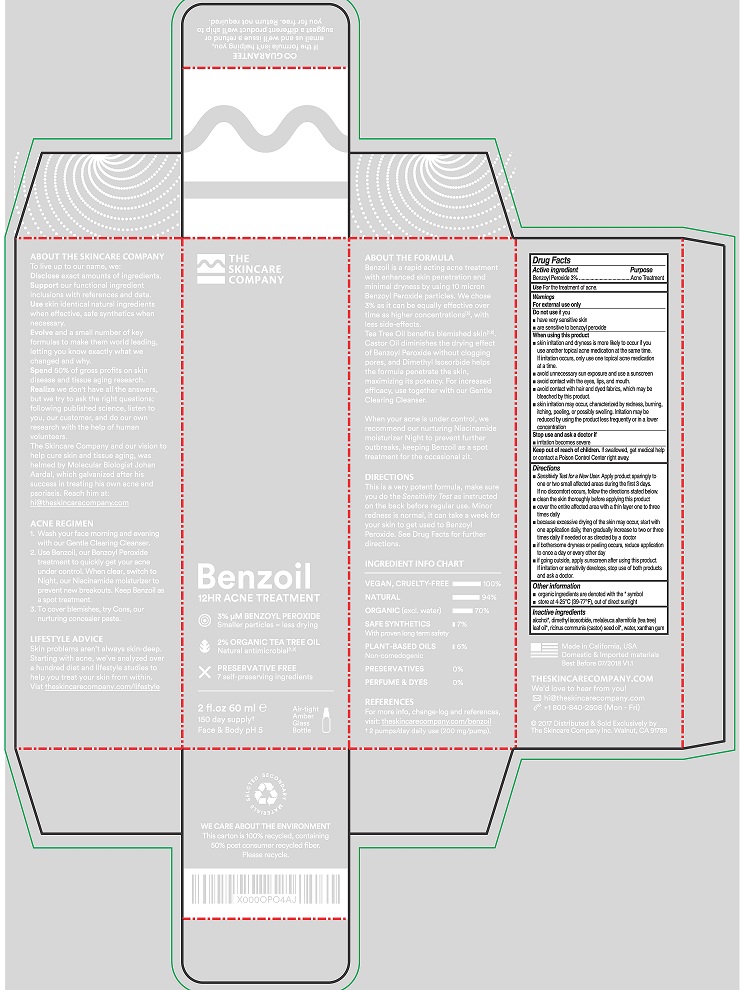 DRUG LABEL: BENZOIL 12HR ACNE TREATMENT
NDC: 71792-101 | Form: LOTION
Manufacturer: THE SKINCARE COMPANY, INC.
Category: otc | Type: HUMAN OTC DRUG LABEL
Date: 20240107

ACTIVE INGREDIENTS: BENZOYL PEROXIDE 3 g/100 mL
INACTIVE INGREDIENTS: ALCOHOL; DIMETHYL ISOSORBIDE; MELALEUCA ALTERNIFOLIA LEAF; CASTOR OIL; WATER; XANTHAN GUM

THE SKINCARE COMPANY - BENZOIL 12HR ACNE TREATMENT (71792-101)

ACTIVE INGREDIENT

BENZOYL PEROXIDE 3%

PURPOSE

ACNE TREATMENT

USE

FOR THE TREATMENT OF ACNE.

WARNINGS

FOR EXTERNAL USE ONLY

WHEN USING THIS PRODUCT

- SKIN IRRITATION AND DRYNESS IS MORE LIKELY TO OCCUR IF YOU USE ANOTHER TOPICAL ACNE MEDICATION AT THE SAME TIME. IF IRRITATION OCCURS, ONLY USE ONE TOPICAL ACNE MEDICATION AT A TIME.
- AVOID UNNECESSARY SUN EXPOSURE AND USE A SUNSCREEN.
- AVOID CONTACT WITH THE EYES, LIPS, AND MOUTH.
- AVOID CONTACT WITH HAIR AND DYED FABRICS, WHICH MAY BE BLEACHED BY THIS PRODUCT.
- SKIN IRRITATION MAY OCCUR, CHARACTERIZED BY REDNESS, BURNING, ITCHING, PEELING, OR POSSIBLY SWELLING. IRRITATION MAY BE REDUCED BY USING THE PRODUCT LESS FREQUENTLY OR IN A LOWER CONCENTRATION.

STOP USE AND ASK A DOCTOR IF

- IRRITATION BECOMES SEVERE.

KEEP OUT OF REACH OF CHILDREN. IF SWALLOWED, GET MEDICAL HELP OR CONTACT A POISON CONTROL CENTER RIGHT AWAY.

DIRECTIONS

- SENSITIVITY TEST FOR A NEW USER. APPLY PRODUCT SPARINGLY TO ONE OR TWO SMALL AFFECTED AREAS DURING THE FIRST 3 DAYS. IF NO DISCOMFORT OCCURS, FOLLOW THE DIRECTIONS STATED BELOW.
- CLEAN THE SKIN THOROUGHLY BEFORE APPLYING THIS PRODUCT.
- COVER THE ENTIRE AFFECTED AREA WITH A THIN LAYER ONE TO THREE TIMES DAILY.
- BECAUSE EXCESSIVE DRYING OF THE SKIN MAY OCCUR, START WITH ONE APPLICATION DAILY, THEN GRADUALLY INCREASE TO TWO OR THREE TIMES DAILY IF NEEDED OR AS DIRECTED BY A DOCTOR.
- IF BOTHERSOME DRYNESS OR PEELING OCCURS, REDUCE APPLICATION TO ONCE A DAY OR EVERY OTHER DAY.
- IF GOING OUTSIDE, APPLY SUNSCREEN AFTER USING THIS PRODUCT. IF IRRITATION OR SENSITIVITY DEVELOPS, STOP USE OF BOTH PRODUCTS AND ASK A DOCTOR.

OTHER INFORMATION

- ORGANIC INGREDIENTS ARE DENOTED WITH THE * SYMBOL
- STORE AT 4-25°c (39-77°f), OUT OF DIRECT SUNLIGHT

INACTIVE INGREDIENTS

ALCOHOL*, DIMETHYL ISOSORBIDE, MELALEUCA ALTERNIFOLIA (TEA TREE) LEAF OIL*, RICINUS COMMUNIS (CASTOR) SEED OIL*, WATER, XANTHAN GUM